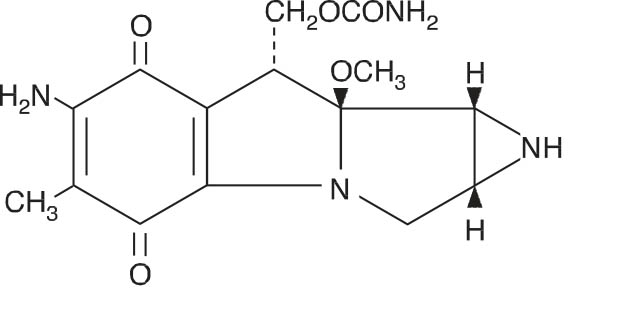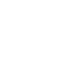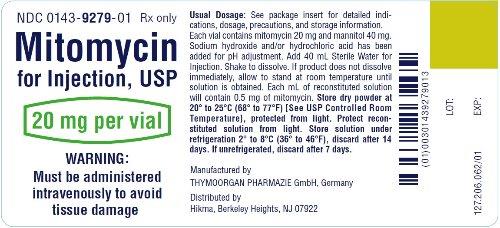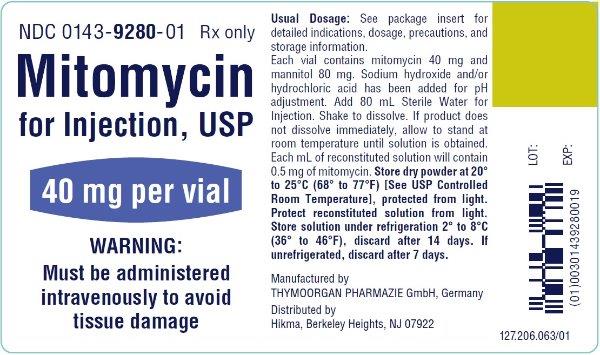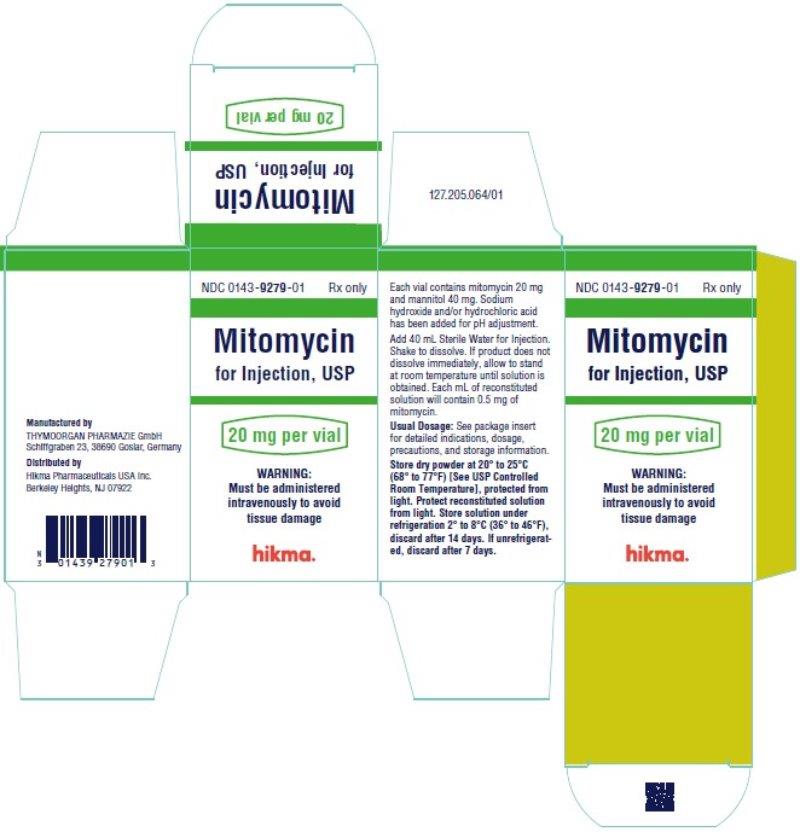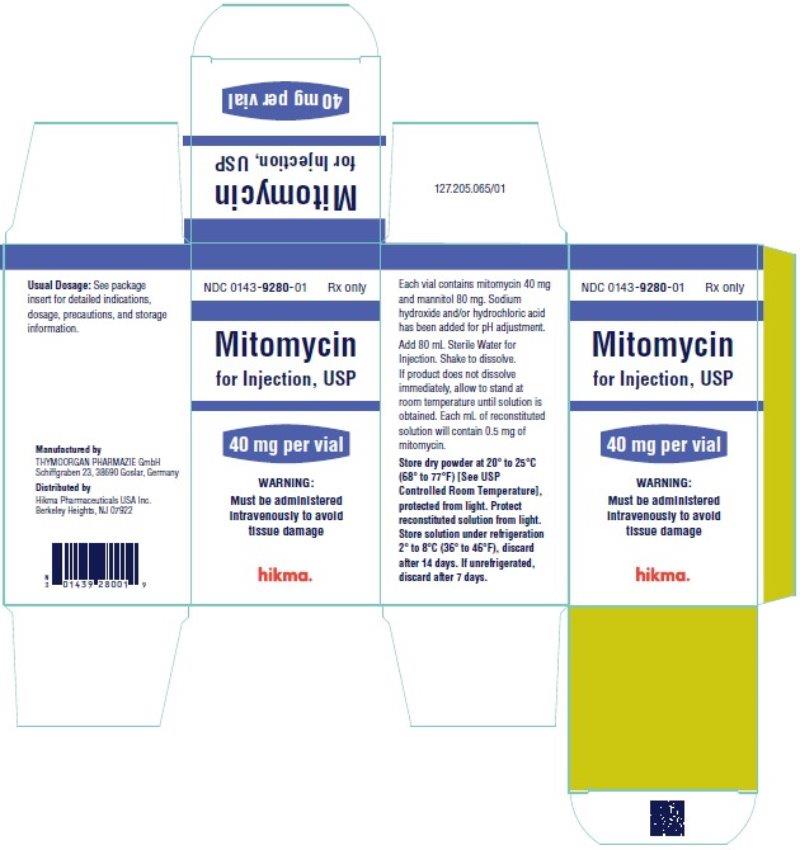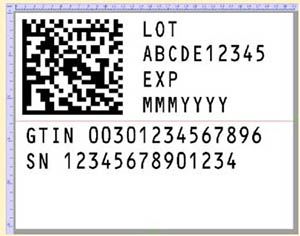 DRUG LABEL: Mitomycin
NDC: 0143-9279 | Form: INJECTION, POWDER, LYOPHILIZED, FOR SOLUTION
Manufacturer: Hikma Pharmaceuticals USA Inc.
Category: prescription | Type: HUMAN PRESCRIPTION DRUG LABEL
Date: 20230515

ACTIVE INGREDIENTS: MITOMYCIN 20 mg/40 mL
INACTIVE INGREDIENTS: MANNITOL 40 mg/40 mL

MITOMYCIN FOR INJECTION, USP

Rx only

WARNINGS

Mitomycin should be administered under the supervision of a qualified physician experienced in the use of cancer chemotherapeutic agents. Appropriate management of therapy and complications is possible only when adequate diagnostic and treatment facilities are readily available.

Bone marrow suppression, notably thrombocytopenia and leukopenia, which may contribute to overwhelming infections in an already compromised patient, is the most common and severe of the toxic effects of mitomycin (see “WARNINGS” and “ADVERSE REACTIONS” Sections).

Hemolytic Uremic Syndrome (HUS) a serious complication of chemotherapy, consisting primarily of microangiopathic hemolytic anemia, thrombocytopenia, and irreversible renal failure, has been reported in patients receiving systemic mitomycin. The syndrome may occur at any time during systemic therapy with mitomycin as a single agent or in combination with other cytotoxic drugs; however, most cases occur at doses ≥ 60 mg of mitomycin. Blood product transfusion may exacerbate the symptoms associated with this syndrome.

The incidence of the syndrome has not been defined.

DESCRIPTION

Mitomycin (also known as mitomycin-C) is an antibiotic isolated from the broth of Streptomyces caespitosus which has been shown to have antitumor activity. The compound is heat stable, has a high melting point, and is freely soluble in organic solvents.

Mitomycin for Injection, USP is a sterile dry mixture of mitomycin and mannitol, which, when reconstituted with Sterile Water for Injection, provides a solution for intravenous administration. Each vial contains either mitomycin 20 mg and mannitol 40 mg or mitomycin 40 mg and mannitol 80 mg.

Mitomycin Structural Formula

C15H18N4O5 M.W. = 334.33

CLINICAL PHARMACOLOGY

Mitomycin selectively inhibits the synthesis of deoxyribonucleic acid (DNA). The guanine and cytosine content correlates with the degree of mitomycin-induced cross-linking. At high concentrations of the drug, cellular RNA and protein synthesis are also suppressed.

In humans, mitomycin is rapidly cleared from the serum after intravenous administration. Time required to reduce the serum concentration by 50% after a 30 mg bolus injection is 17 minutes. After injection of 30 mg, 20 mg, or 10 mg IV, the maximal serum concentrations were 2.4 mcg/mL,

1.7 mcg/mL, and 0.52 mcg/mL, respectively. Clearance is affected primarily by metabolism in the liver, but metabolism occurs in other tissues as well. The rate of clearance is inversely proportional to the maximal serum concentration because, it is thought, of saturation of the degradative pathways.

Approximately 10% of a dose of mitomycin is excreted unchanged in the urine. Since metabolic pathways are saturated at relatively low doses, the percent of a dose excreted in urine increases with increasing dose. In children, excretion of intravenously administered mitomycin is similar.

Animal Toxicology

Mitomycin has been found to be carcinogenic in rats and mice. At doses approximating the recommended clinical dose in man, it produces a greater than 100% increase in tumor incidence in male Sprague-Dawley rats, and a greater than 50% increase in tumor incidence in female Swiss mice.

INDICATIONS AND USAGE

Mitomycin for Injection, USP is not recommended as single-agent, primary therapy. It has been shown to be useful in the therapy of disseminated adenocarcinoma of the stomach or pancreas in proven combinations with other approved chemotherapeutic agents and as palliative treatment when other modalities have failed. Mitomycin is not recommended to replace appropriate surgery and/or radiotherapy.

CONTRAINDICATIONS

Mitomycin is contraindicated in patients who have demonstrated a hypersensitive or idiosyncratic reaction to it in the past.

Mitomycin is contraindicated in patients with thrombocytopenia, coagulation disorder, or an increase in bleeding tendency due to other causes.

WARNINGS

Patients being treated with mitomycin must be observed carefully and frequently during and after therapy.

The use of mitomycin results in a high incidence of bone marrow suppression, particularly thrombocytopenia and leukopenia. Therefore, the following studies should be obtained repeatedly during therapy and for at least 8 weeks following therapy: platelet count, white blood cell count, differential, and hemoglobin. The occurrence of a platelet count below 100,000/mm^3 or a WBC below 4,000/mm^3 or a progressive decline in either is an indication to withhold further therapy until blood counts have recovered above these levels.

Patients should be advised of the potential toxicity of this drug, particularly bone marrow suppression. Deaths have been reported due to septicemia as a result of leukopenia due to the drug.

Patients receiving mitomycin should be observed for evidence of renal toxicity. Mitomycin should not be given to patients with a serum creatinine greater than 1.7 mg percent.

Usage in Pregnancy

Safe use of mitomycin in pregnant women has not been established. Teratological changes have been noted in animal studies. The effect of mitomycin on fertility is unknown.

PRECAUTIONS

Acute shortness of breath and severe bronchospasm have been reported following the administration of vinca alkaloids in patients who had previously or simultaneously received mitomycin. The onset of this acute respiratory distress occurred within minutes to hours after the vinca alkaloid injection. The total number of doses for each drug has varied considerably. Bronchodilators, steroids and/or oxygen have produced symptomatic relief.

A few cases of adult respiratory distress syndrome have been reported in patients receiving mitomycin in combination with other chemotherapy and maintained at FlO2 concentrations greater than 50% perioperatively. Therefore, caution should be exercised using only enough oxygen to provide adequate arterial saturation since oxygen itself is toxic to the lungs. Careful attention should be paid to fluid balance and overhydration should be avoided.

Bladder fibrosis/contraction has been reported with intravesical administration (not an approved route of administration), which in rare cases has required cystectomy.

Nursing Mothers

It is not known if mitomycin is found in human milk. Because many drugs are found in milk, it is recommended that women receiving mitomycin not breast feed because of the potential for serious adverse reactions from mitomycin in nursing infants.

Pediatric Use

Safety and effectiveness in pedriatric patients have not been established.

ADVERSE REACTIONS

Bone Marrow Toxicity

This was the most common and most serious toxicity, occurring in 605 of 937 patients (64.4%). Thrombocytopenia and/or leukopenia may occur anytime within 8 weeks after onset of therapy with an average time of 4 weeks. Recovery after cessation of therapy was within 10 weeks. About 25% of the leukopenic or thrombocytopenic episodes did not recover. Mitomycin produces cumulative myelosuppression.

Integument and Mucous Membrane Toxicity

This has occurred in approximately 4% of patients treated with mitomycin. Cellulitis at the injection site has been reported and is occasionally severe. Stomatitis and alopecia also occur frequently. Rashes are rarely reported. The most important dermatological problem with this drug, however, is the necrosis and consequent sloughing of tissue which results if the drug is extravasated during injection. Extravasation may occur with or without an accompanying stinging or burning sensation and even if there is adequate blood return when the injection needle is aspirated. There have been reports of delayed erythema and/or ulceration occurring either at or distant from the injection site, weeks to months after mitomycin, even when no obvious evidence of extravasation was observed during administration. Skin grafting has been required in some cases.

Renal Toxicity

2% of 1,281 patients demonstrated a statistically significant rise in creatinine. There appeared to be no correlation between total dose administered or duration of therapy and the degree of renal impairment.

Pulmonary Toxicity

This has occurred infrequently but can be severe and may be life-threatening. Dyspnea with a nonproductive cough and radiographic evidence of pulmonary infiltrates may be indicative of mitomycin-induced pulmonary toxicity. If other etiologies are eliminated, mitomycin therapy should be discontinued. Steroids have been employed as treatment of this toxicity, but the therapeutic value has not been determined. A few cases of adult respiratory distress syndrome have been reported in patients receiving mitomycin in combination with other chemotherapy and maintained at FlO2 concentrations greater than 50% perioperatively.

Hemolytic Uremic Syndrome (HUS)

This serious complication of chemotherapy, consisting primarily of microangiopathic hemolytic anemia (hematocrit ≤ 25%), thrombocytopenia (≤ 100,000/mm^3), and irreversible renal failure (serum creatinine ≥ 1.6 mg/dL) has been reported in patients receiving systemic mitomycin. Microangiopathic hemolysis with fragmented red blood cells on peripheral blood smears has occurred in 98% of patients with the syndrome. Other less frequent complications of the syndrome may include pulmonary edema (65%), neurologic abnormalities (16%), and hypertension. Exacerbation of the symptoms associated with HUS has been reported in some patients receiving blood product transfusions. A high mortality rate (52%) has been associated with this syndrome.

The syndrome may occur at any time during systemic therapy with mitomycin as a single agent or in combination with other cytotoxic drugs. Less frequently, HUS has also been reported in patients receiving combinations of cytotoxic drugs not including mitomycin. Of 83 patients studied, 72 developed the syndrome at total doses exceeding 60 mg of mitomycin. Consequently, patients receiving ≥ 60 mg of mitomycin should be monitored closely for unexplained anemia with fragmented cells on peripheral blood smear, thrombocytopenia, and decreased renal function.

The incidence of the syndrome has not been defined.

Therapy for the syndrome is investigational.

Cardiac Toxicity

Congestive heart failure, often treated effectively with diuretics and cardiac glycosides, has rarely been reported. Almost all patients who experienced this side effect had received prior doxorubicin therapy.

Acute Side Effects Due to Mitomycin were fever, anorexia, nausea, and vomiting. They occurred in about 14% of 1,281 patients.

Other

Headache, blurring of vision, confusion, drowsiness, syncope, fatigue, edema, thrombophlebitis, hematemesis, diarrhea, and pain. These did not appear to be dose related and were not unequivocally drug related. They may have been due to the primary or metastatic disease processes. Malaise and asthenia have been reported as part of postmarketing surveillance. Bladder fibrosis/contraction has been reported with intravesical administration (see PRECAUTIONS).

DOSAGE AND ADMINISTRATION

Mitomycin should be given intravenously only, using care to avoid extravasation of the compound. If extravasation occurs, cellulitis, ulceration, and slough may result.

Each vial contains either mitomycin 20 mg and mannitol 40 mg or mitomycin 40 mg and mannitol 80 mg. To administer, add Sterile Water for Injection 40 mL or 80 mL, respectively. Shake to dissolve. If product does not dissolve immediately, allow to stand at room temperature until solution is obtained.

After full hematological recovery (see guide to dosage adjustment) from any previous chemotherapy, the following dosage schedule may be used at 6- to 8-week intervals:

20 mg/m^2 intravenously as a single dose via a functioning intravenous catheter.

Because of cumulative myelosuppression, patients should be fully reevaluated after each course of mitomycin, and the dose reduced if the patient has experienced any toxicities. Doses greater than 20 mg/m^2 have not been shown to be more effective and are more toxic than lower doses.

The following schedule is suggested as a guide to dosage adjustment:

Nadir After Prior Dose |  | Percentage of Prior Dose To Be Given
Leukocytes/mm^3 | Platelets/mm^3
>4000 | >100,000 | 100%
3000 to 3999 | 75,000 to 99,999 | 100%
2000 to 2999 | 25,000 to 74,999 | 70%
<2000 | <25,000 | 50%

No repeat dosage should be given until leukocyte count has returned to 4000/mm^3 and platelet count to 100,000/mm^3.

When mitomycin is used in combination with other myelosuppressive agents, the doses should be adjusted accordingly. If the disease continues to progress after two courses of mitomycin, the drug should be stopped since chances of response are minimal.

Stability

1. Unreconstituted mitomycin stored at controlled room temperature is stable for the lot life indicated on the package. Avoid excessive heat (over 40°C).

2. Reconstituted with Sterile Water for Injection to a concentration of 0.5 mg per mL, mitomycin is stable for 14 days refrigerated or 7 days at room temperature. Protect reconstituted solution from light.

3. Diluted in various IV fluids at room temperature, to a concentration of 20 to 40 micrograms per mL:

IV Fluid | Stability
5% Dextrose Injection | 3 hours
0.9% Sodium Chloride Injection | 12 hours
Sodium Lactate Injection | 24 hours

4. The combination of mitomycin (5 mg to 15 mg) and heparin (1,000 units to 10,000 units) in 30 mL of 0.9% Sodium Chloride Injection is stable for 48 hours at room temperature.

Procedures For Proper Handling and Disposal of anticancer drugs should be considered. Several guidelines on this subject have been published.^1-7 There is no general agreement that all of the procedures recommended in the guidelines are necessary or appropriate.

Parenteral drug products should be inspected visually for particulate matter and discoloration prior to administration, whenever solution and container permit.

HOW SUPPLIED

Mitomycin for Injection, USP is supplied in the following package strengths:

NDC 0143-9279-01 20 mg; individually-boxed vial

NDC 0143-9280-01 40 mg; individually-boxed vial

Store dry powder at 20° to 25°C (68° to 77°F) [See USP Controlled Room Temperature], protected from light.

To report SUSPECTED ADVERSE REACTIONS, contact Hikma Pharmaceuticals USA Inc. at 1-877-845-0689, or the FDA at 1-800-FDA-1088 or www.fda.gov/medwatch.

For Product Inquiry call 1-877-845-0689.

REFERENCES

- 1.Recommendations for the Safe Handling of Parenteral Antineoplastic Drugs. NIH Publication No. 83-2621. For sale by the Superintendent of Documents, U.S. Government Printing Office, Washington, D.C. 20402.
- 2.AMA Council Report. Guidelines for Handling Parenteral Antineoplastics, JAMA. 1985; 253(11):1590–1592.
- 3.National Study Commission on Cytotoxic Exposure—Recommendations for Handling Cytotoxic Agents. Available from Louis P. Jeffrey, Sc.D., Chairman, National Study Commission on Cytotoxic Exposure, Massachusetts College of Pharmacy and Allied Sciences, 179 Longwood Avenue, Boston, Massachusetts 02115.
- 4.Clinical Oncological Society of Australia: Guidelines and Recommendations for Safe Handling of Antineoplastic Agents. Med J Australia. 1983; 1:426–428.
- 5.Jones, RB, et al. Safe Handling of Chemotherapeutic Agents: A Report from the Mount Sinai Medical Center. Ca—A Cancer J for Clinicians. 1983; Sept./Oct., 258–263.
- 6.American Society of Hospital Pharmacists Technical Assistance Bulletin on Handling Cytotoxic and Hazardous Drugs. Am J Hosp Pharm. 1990; 47:1033–1049.
- 7.Controlling Occupational Exposure to Hazardous Drugs. (OSHA WORK-PRACTICE GUIDELINES). Am J Health-Syst Pharm 1996; 53: 1669-1685.

Manufactured by
THYMOORGAN PHARMAZIE GmbH,
Schiffgraben 23, 38690 Goslar, Germany

Distributed by
Hikma Pharmaceuticals USA Inc.
Berkeley Heights, NJ 07922

Revised July 2020

127.207.030/01

Vial Label - 20 mg

NDC 0143-9279-01 Rx only
Mitomycin
for Injection, USP
20 mg per vial
WARNING:
Must be administered
intravenously to avoid
tissue damage

Vial Label - 40 mg

NDC 0143-9280-01 Rx only
Mitomycin
for Injection, USP
40 mg per vial
WARNING:
Must be administered
intravenously to avoid
tissue damage

Carton Label - 20 mg

NDC 0143-9279-01 Rx only
Mitomycin
for Injection, USP
20 mg per vial
WARNING:
Must be administered
intravenously to avoid
tissue damage

Carton Label - 40 mg

NDC 0143-9280-01 Rx only
Mitomycin
for Injection, USP
40 mg per vial
WARNING:
Must be administered
intravenously to avoid
tissue damage

Serialization Image

Representative Carton Serialization Image